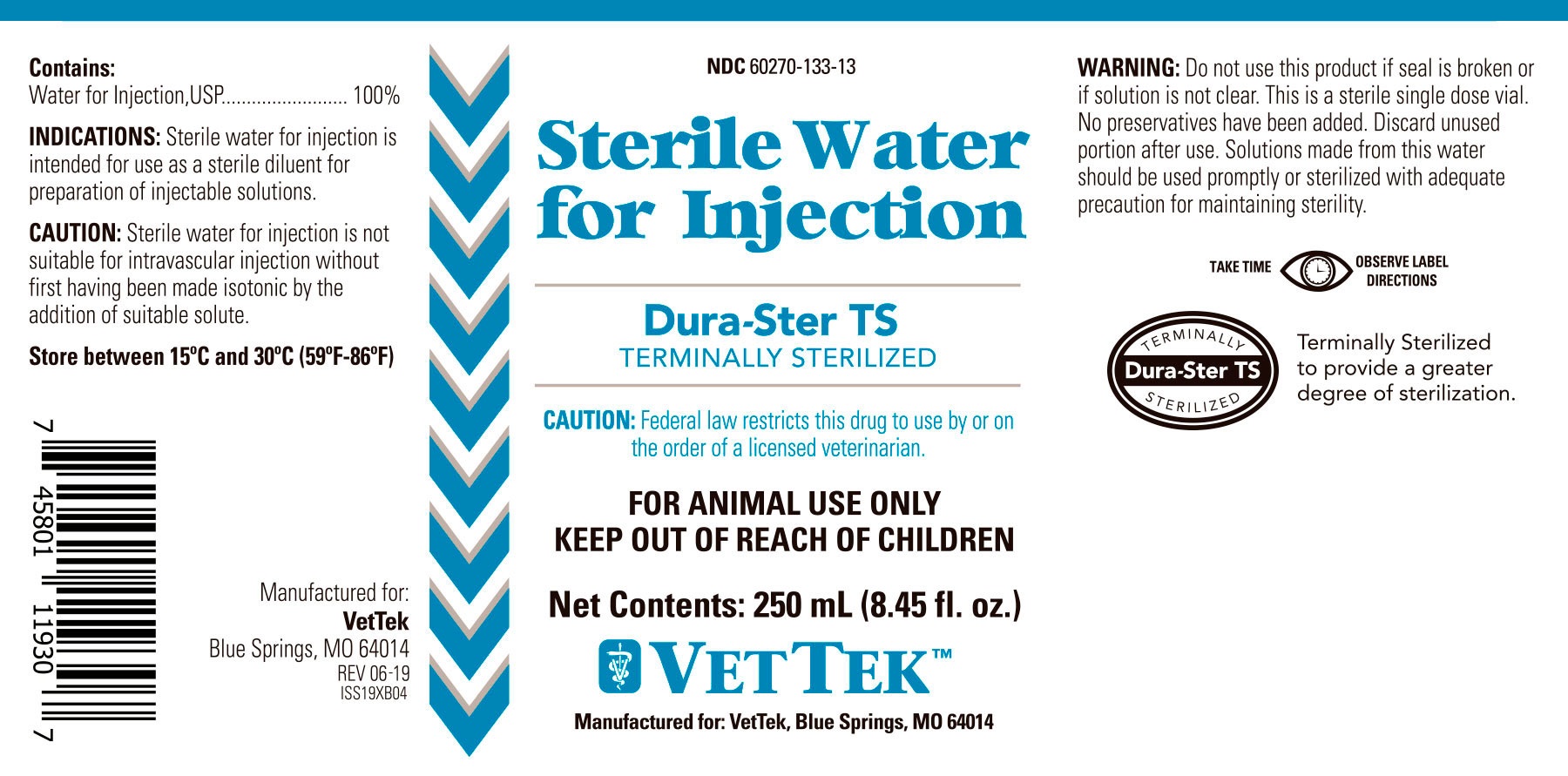 DRUG LABEL: Sterile Water
NDC: 60270-133 | Form: INJECTION
Manufacturer: VetTek
Category: animal | Type: PRESCRIPTION ANIMAL DRUG LABEL
Date: 20191223

ACTIVE INGREDIENTS: WATER 100 mL/100 mL

STERILE WATER FOR INJECTION

STERILE WATER- sterile water for injection

ACTIVE INGREDIENT

Contains:

Water For Injection, USP................ 100%

INDICATIONS:

Sterile water for injection is intended for use as a sterile diluent for preparation of injectable solutions.

CAUTION:

Sterile water for injection is not suitable for intravascular injection without first having been made isotonic by the addition of suitable solute.

STORAGE

Store between 15°C and 30°C (59°F-86°F).

KEEP OUT OF REACH OF CHILDREN

CAUTION:

Federal law restricts this drug to use by or on the order of a licensed veterinarian.

WARNING:

Do not use this product if seal is broken or if solution is not clear. This is a sterile single dose vial. No preservatives have been added. Discard unused portion after use. Solutions made from this water should be used promptly or sterilized with adequate precautions for maintaining sterility.

DOSAGE AND ADMINISTRATION

TAKE TIME OBSERVE LABEL DIRECTIONS.

Terminally Sterilized to provide a greated degree of sterilization.

INFORMATION FOR OWNERS/CAREGIVERS

Manufactured for:

VetTek

Blue Springs, MO, 64014

REV 06-19

ISS19XB04

PRINCIPAL DISPLAY PANEL

NDC 60270-133-13

Sterile Water for Injection

Dura-Ster TS

TERMINALLY STERILIZED

CAUTION: Federal law restricts this drug to use by or on the order of a licensed veterinarian.

FOR ANIMAL USE ONLY

KEEP OUT OF REACH OF CHILDREN

Net Contents: 250 mL (8.45 fl. oz.)

VETTEKTM

Manufactured for: VetTek, Blue Springs, MO, 64014